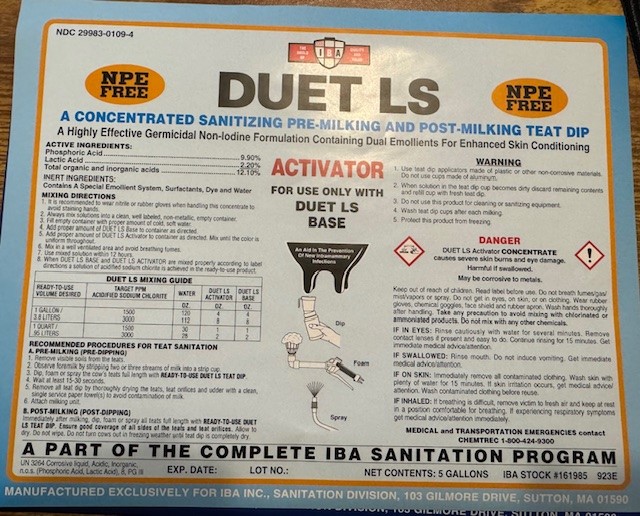 DRUG LABEL: DUET LS ACTIVATOR
NDC: 29983-0109 | Form: SOLUTION
Manufacturer: IBA
Category: animal | Type: OTC ANIMAL DRUG LABEL
Date: 20241226

ACTIVE INGREDIENTS: LACTIC ACID 22 g/1 L; PHOSPHORIC ACID 99 g/1 L
INACTIVE INGREDIENTS: FD&C BLUE NO. 1; BENZENESULFONIC ACID; GLYCERIN; SODIUM HYDROXIDE; TRIETHANOLAMINE

DUET LS A CONCENTRATED SANITIZING PRE-MILKING AND POST-MILKING TEAT DIP
A HIGHLY EFFECTIVE GERMICIDAL NON-IODINE FORMULATION CONTAINING DUAL EMOLLIENTS FOR ENHANCED SKIN CONDITIONING
FOR USE ONLY WITH DUET BASE

ACTIVE INGREDIENT

Phosphoric Acid 9.9%

Lactic Acid 2.2%

Total Organic and inorganic acids...........................12.10%

INERT INGREDIENTS:

CONTAINS A SPECIAL EMOLLIENT SYSTEM,SURFACTANTS, DYE AND WATER

INDICATIONS AND USAGE

MIXING DIRECTIONS:

1. It is recommended to ear nitrile or rubber gloves when handling this concentrate to avoid staining hands.

2. Always mix solutions into clean, well labeled, non-metallic, empty container.

3. Fill empty container with proper amount of cold, soft water.

4. Add proper amount of DUET LS Base to container as directed.

5. Add proper amount of DUET LS Activator to container as directed. Mix until the color is uniform throughout.

6. Mix in a well ventilated area and avoid breathing fumes.

7. Use mixed solution within 12hrs.

8. When DUET LS BASE and DUET LS ACTIVATOR are mixed properly according to label directions a solution of acidified sodium chlorite is achieved in the ready to use product.

DUET MIXING GUIDE

Ready-To-Use Volume Desired Target PPM ACIDIFIED SODIUM CHLORITE Water (oz) Duet Activator (oz) Duet Base (oz)

1 Gallon/3.8Liters 1500 120 4 4

3000 112 8 8

1 Quart/.95 Liters 1500 30 1 1

3000 28 2 2

RECOMMENDED PROCEDURES FOR TEAT SANITATION
A. PRE-MILKING (PRE-DIPPING)
1. REMOVE VISIBLE SOILS FROM THE TEATS.
2. OBSERVE FOREMILK BY STRIPPING TWO OR THREE STREAMS OF MILK INTO A STRIP CUP.
3. DIP, FOAM or SPRAY THE COW'S TEATS FULL LENGTH WITH READY-TO-USE DUET LS TEAT DIP.
4 WAIT APPROXIMATELY 15-30 SECONDS.
5. REMOVE ALL TEAT DIP BY THOROUGHLY DRYING THE TEATS AND TEAT ORIFICES AND UDDER (IF SPRAYING), WITH A CLEAN, SINGLE SERVICE PAPER TOWEL(S).
6. ATTACH MILKING UNIT
B. POST-MILKING (POST DIPPING)
Immediately after milking dip, foam or spray all teats full length with READY-TO-USE DUET LS TEAT DIP. Ensure good coverage of all sides of the teats and teat orifices. Allow to dry. Do not wipe. Do not turn cows out in freezing weather until teat dip is completely dry.

WARNING

1. Use teat dip applicators made of plastic or other non-corrosive materials. Do not use cups made of aluminum.

2. When solution in the teat dip cup becomes dirty discard remaining contents and refill cup with fresh teat dip.

3. Do not use this product for cleaning or sanitizing equipment.

4. Wash teat dip cups after each milking.

5. Protest this product from freezing.

FIRST AID PROCEDURES

Keep out of children. Read label before use. Do not breath fumes/gas/mist/vapors or spray. Do not get in eyes, on skin, or on clothing. Wear rubber gloves, chemicl goggles, face shield and rubber apron. Wash hands thoroughly after handling. Take any precaution to avoid mixing with chlorinated or ammoniated products. Do not mix with any other chemicals.

IF IN EYES: RINSE CAUSTIOUSLY WITH FRESH,TEPID WATER FOR SEVERAL MINUTES.REMOVE CONTACT LENSES IF PRESENT AND EASY TO DO. CONTINUE RINSING FOR 15 MINUTES. GET IMMEDIATE MEDICAL ADVICE/ATTENTION.

IF SWALLOWED: RINSE MOUTH. DO NOT INDUCE VOMITING.GET IMMEDIATE MEDICAL ADVISE/ATTENTION.

IF ON SKIN: IMMEDIATELY REMOVE ALL CONTAMINATED CLOTHING.WASH SKIN WITH PLENTY OF WATER FOR 15 MINUTES. IF SKIN IRRITATION OCCURS,GET MEDICAL ADVICE/ATTENTION. WASH CONTAMINATED CLOTHING BEFORE REUSE.

IF INHALED: IF BREATHING IS DIFFICULT,REMOVE VICTIM TO FRESH AIR AND KEEP AT REST IN A POSITION COMFORTABLE FOR BREATHING. IF EXPERIENCING RESPIRATORY SYMPTOMS GET MEDICAL ADVICE/ATTENTION IMMEDIATELY.

ALWAYS SEEK IMMEDIATE MEDICAL ATTENTION

FOR MEDICAL EMERGENCIES CALL 1-800-424-9300